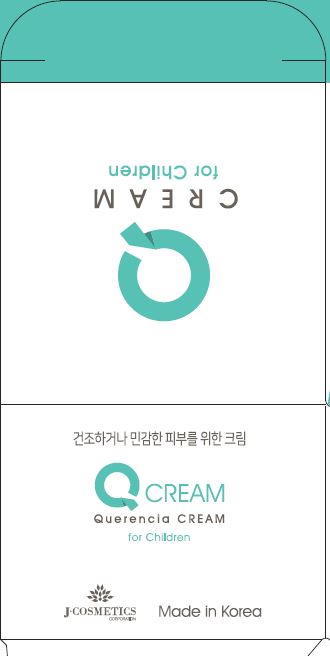 DRUG LABEL: Querencia Creamfor Children
NDC: 70488-0010 | Form: CREAM
Manufacturer: MUSEE Cosmetic Co.,Ltd.
Category: otc | Type: HUMAN OTC DRUG LABEL
Date: 20190104

ACTIVE INGREDIENTS: DIMETHICONE 8 g/100 mL
INACTIVE INGREDIENTS: WATER; BUTYLENE GLYCOL

Drug Facts

ACTIVE INGREDIENT

dimethicone

INACTIVE INGREDIENT

Water, Butylene Glycol, ButyrospermumParkii (Shea Butter), Glycerin, SparassisCrispa Extract, Betaine, Theobroma Cacao (Cocoa) Seed Butter, Beeswax, Bentonite, Hydrogenated Polydecene, Olea Europaea (Olive) Fruit Oil, Caprylic/Capric Triglyceride, Squalane, Portulaca Oleracea Extract, Hydrogenated Polyisobutene, Cetearyl Alcohol, Stearyl alcohol, Glyceryl Stearate SE, Arginine, Potassium Cetyl Phosphate, Stearic Acid, Caprylyl Glycol, Hydrogenated Palm Glycerides, Polyisobutene, Cyclohexasiloxane, Cyclopentasiloxane, Acrylates/C10-30 Alkyl Acrylate Crosspolymer, Ethylhexylglycerin, Dimethicone/Vinyl DimethiconeCrosspolymer, Polyacrylate-13, 1,2-Hexanediol, Tromethamine, Polysorbate 20, Disodium EDTA

PURPOSE

for sensitive and dry skin

keep out of reach of the children

INDICATIONS AND USAGE

Apply to the skin and gently rub it to absorb it

WARNINGS

1. Do not use in the following cases(Eczema and scalp wounds)
2.Side Effects
1)Due to the use of this druf if rash, irritation, itching and symptopms of hypersnesitivity occur dicontinue use and consult your phamacisr or doctor
3.General Precautions
1)If in contact with the eyes, wash out thoroughty with water If the symptoms are servere, seek medical advice immediately
2)This product is for exeternal use only. Do not use for internal use
4.Storage and handling precautions
1)If possible, avoid direct sunlight and store in cool and area of low humidity
2)In order to maintain the quality of the product and avoid misuse
3)Avoid placing the product near fire and store out in reach of children

DOSAGE AND ADMINISTRATION

for topical use only